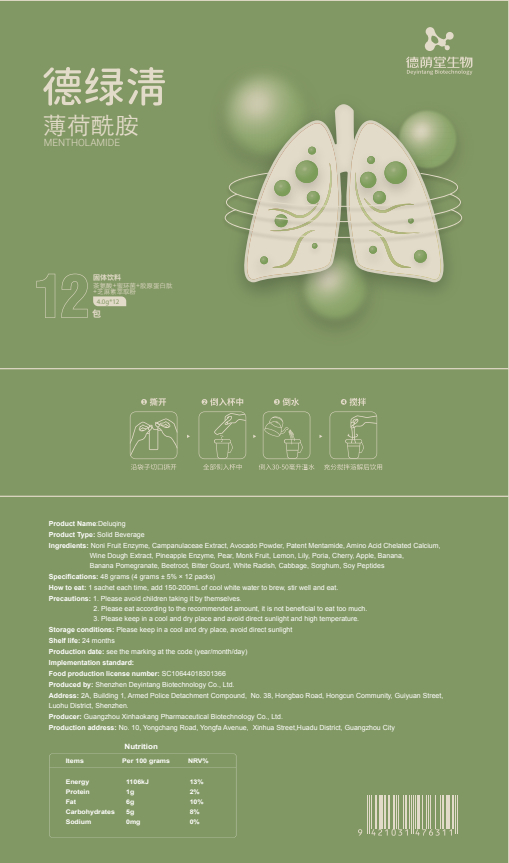 DRUG LABEL: Deluqing
NDC: 82570-015 | Form: POWDER
Manufacturer: Shenzhen Deyintang Biotechnology Co., Ltd.
Category: otc | Type: HUMAN OTC DRUG LABEL
Date: 20220222

ACTIVE INGREDIENTS: GUAVA 2 g/100 g; BEET JUICE 2 g/100 g; MOMORDICA CHARANTIA WHOLE 2 g/100 g; DAIKON 2 g/100 g; SORGHUM 1 g/100 g; SOY PROTEIN 1 g/100 g; AVOCADO 10 g/100 g; TOLUENE 6 g/100 g; SIRAITIA GROSVENORII WHOLE 4 g/100 g; NONI FRUIT 20 g/100 g; CABBAGE 1 g/100 g; PLATYCODON GRANDIFLORUM ROOT 10 g/100 g; BANANA 3 g/100 g; AMINO ACIDS 5 g/100 g; BROMELAINS 5 g/100 g; PEAR 5 g/100 g; LILIUM LANCIFOLIUM WHOLE 3 g/100 g; FU LING 3 g/100 g
INACTIVE INGREDIENTS: CHERRY; APPLE; LEMON

ACTIVE INGREDIENT

Noni Fruit Enzyme,Campanulaceae Extract,Avocado Powder,Patent Mentamide, Amino Acid Chelated Calcium,Wine Dough Extract, Pineapple Enzyme, Pear,Monk Fruit,Lily,Poria,Banana,Banana Pomegranate, Beetroot, Bitter Gourd, White Radish, Cabbage,

Sorghum, Soy Peptides

INACTIVE INGREDIENT

Lemon,Cherry, Apple

PURPOSE

health care

Please avoid children taking it by themselves.

How to eat

1 sachet each time, add 150-200mL of cool white water to brew, stir well and eat.

INDICATIONS AND USAGE

Please eat according to the recommended amount, it is not beneficial to eat too much.

Storage conditions

Please keep in a cool and dry place, avoid direct sunlight

WARNINGS

1.Please avoid children taking it by themselves.
2.Please eat according to the recommended amount, it is not beneficial to eat too much.
3.Please keep in a cool and dry place and avoid direct sunlight and high temperature.